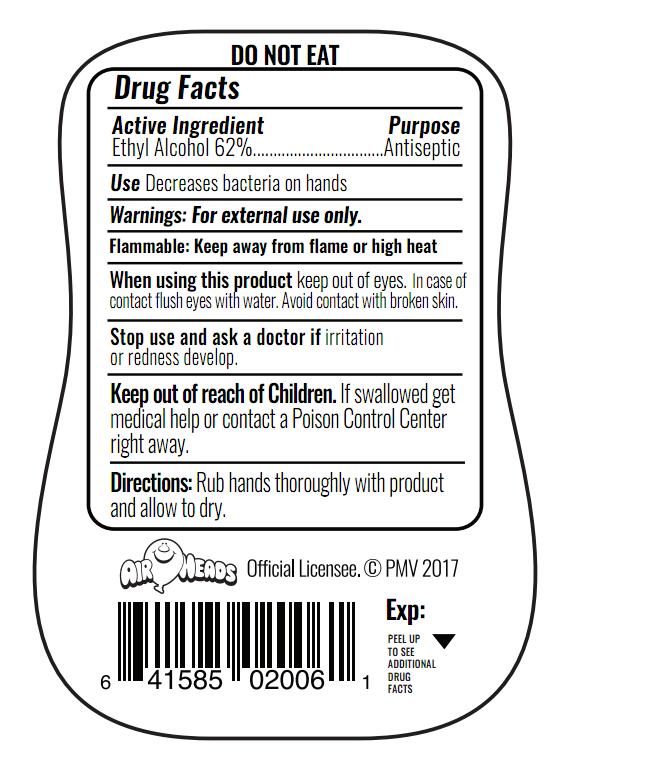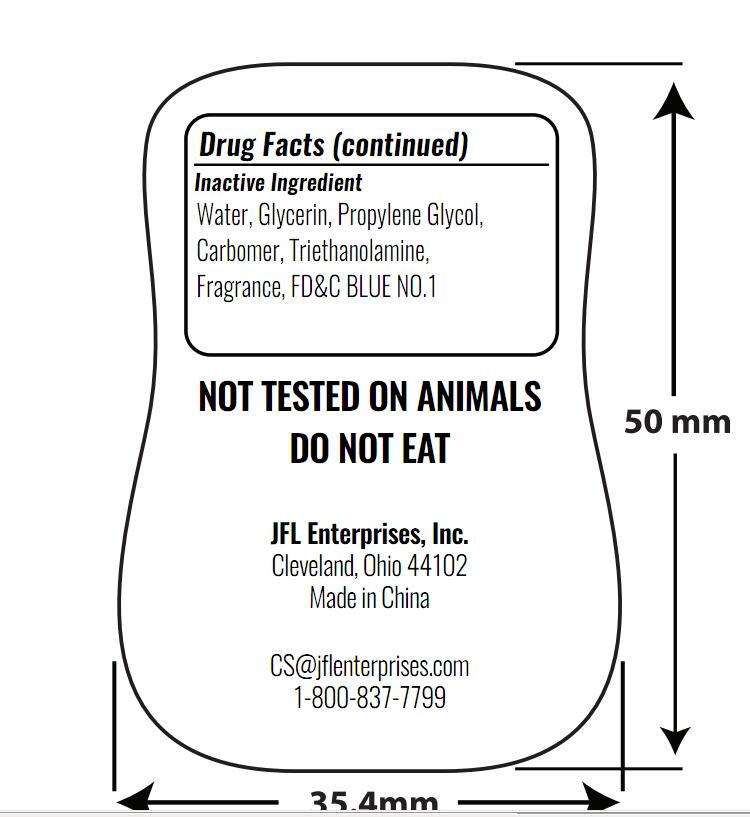 DRUG LABEL: HAND SANITIZER
NDC: 71011-005 | Form: GEL
Manufacturer: NingBo Huize Commodity Co.,Ltd.
Category: otc | Type: HUMAN OTC DRUG LABEL
Date: 20180823

ACTIVE INGREDIENTS: ALCOHOL 62 mL/100 mL
INACTIVE INGREDIENTS: WATER; GLYCERIN; CARBOXYPOLYMETHYLENE; TROLAMINE; PROPYLENE GLYCOL DIACETATE

71011-005 HAND SANITIZER

Active Ingredient

Ethyl Alcohol 62%

Purpose

Antiseptic

Use

Decreases bacteria on hands

Warning

For external use only.
Flammable: Keep away from flame or high heat
When using this product keep out of eyes.In case of contact flush eyes with water. Avoid contact with broken skin.

Stop use and ask a doctor if irritation or redness develop.

Keep out of reach of children .If swallowed ,get medical help or contact a Poison on Control Center immediately

Directions

Rub hands thoroughly with product and allow to dry.

INACTIVE INGREDIENT

Water, Glycerin, Propylene Glycol, Carbomer, Triethanolamine, Fragrance, FD&C BLUE NO.1